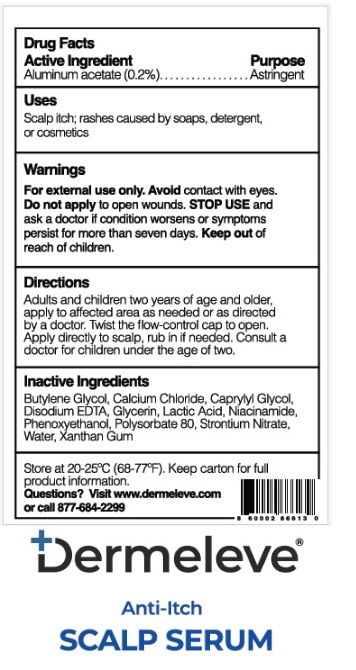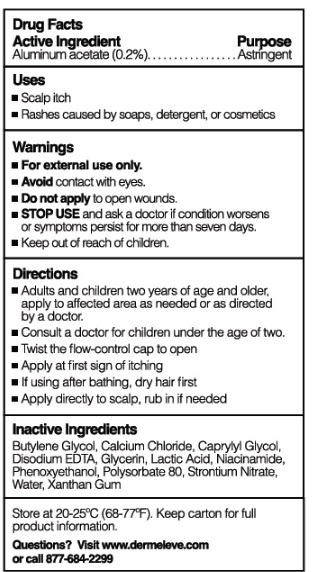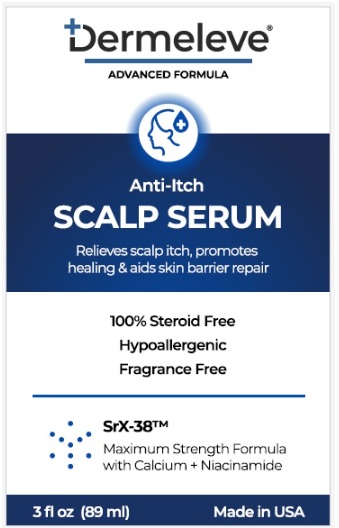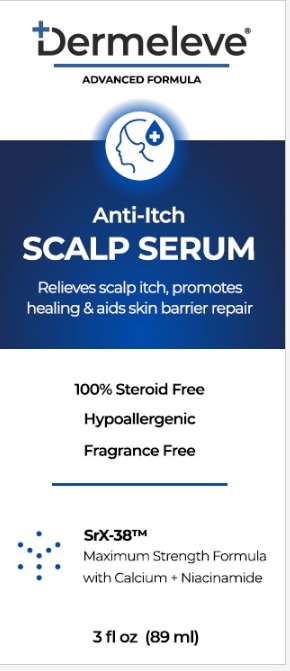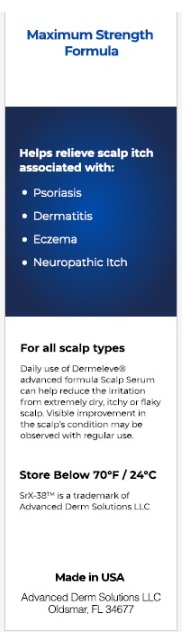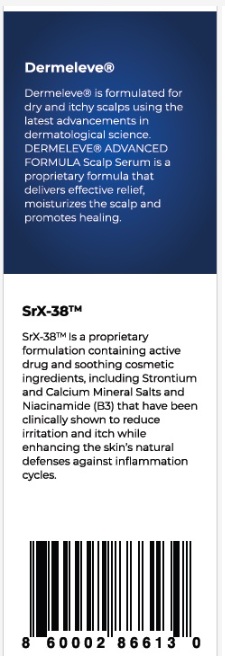 DRUG LABEL: Dermeleve Anti Itch Scalp Serum
NDC: 81507-004 | Form: SOLUTION
Manufacturer: Advanced Derm Solutions LLC
Category: otc | Type: HUMAN OTC DRUG LABEL
Date: 20251007

ACTIVE INGREDIENTS: ALUMINUM ACETATE 0.2 g/100 mL
INACTIVE INGREDIENTS: BUTYLENE GLYCOL; CALCIUM CHLORIDE; CAPRYLYL GLYCOL; EDETATE DISODIUM ANHYDROUS; GLYCERIN; LACTIC ACID; NIACINAMIDE; PHENOXYETHANOL; POLYSORBATE 80; STRONTIUM NITRATE; WATER; XANTHAN GUM

Active Ingredient

Aluminum acetate (0.2%)

Purpose

Astringent

Uses

Scalp itch; rashes caused by soaps, detergent, or cosmetics

Warnings

For external use only. Avoidcontact with eyes. Do not applyto open wounds. STOP USEand ask a doctor if condition worsens or symptoms persist for more than seven days. Keep out of reach of children.

Directions

Adults and children two years of age and older, apply to affected area as needed or as directed by a doctor. Twist the flow-control cap to open. Apply directly to scalp, rub in if needed. Consult a doctor for children under the age of two.

Store at 20-25ºC (68-77ºF). Keep carton for full product information

Questions? Visit www.dermeleve.com or call 877-684-2299

Inactive ingredients

Butylene Glycol, Calcium Chloride, Caprylyl Glycol, Disodium EDTA, Glycerin, Lactic Acid, Niacinamide, Phenoxyethanol, Polysorbate 80, Strontium Nitrate, Water, Xanthan Gum